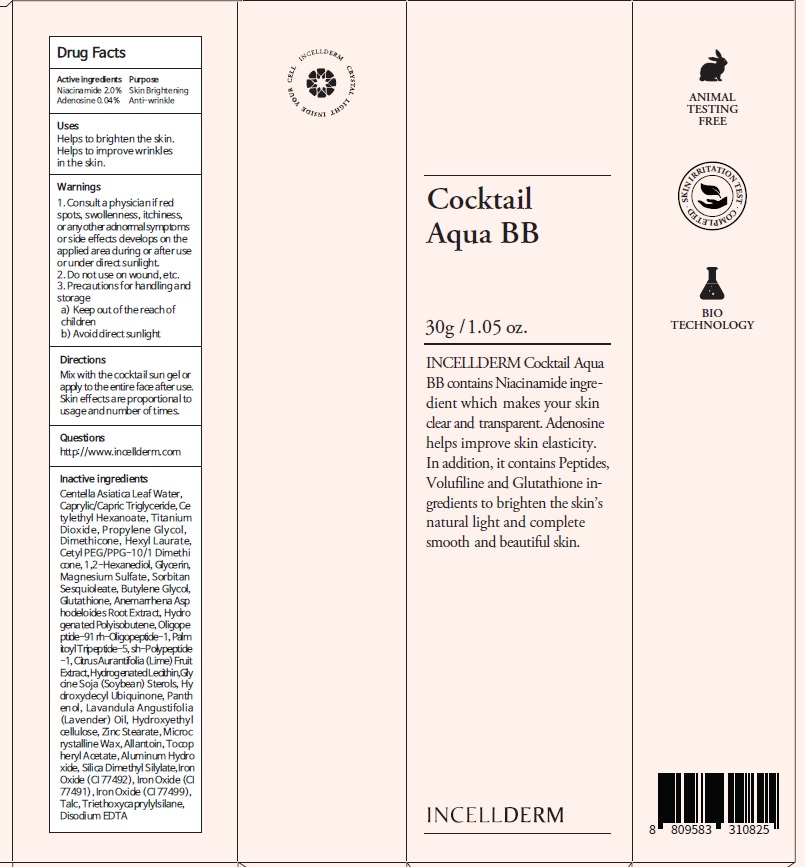 DRUG LABEL: INCELLDERM Cocktail Aqua BB
NDC: 72650-050 | Form: CREAM
Manufacturer: Riman Co., Ltd.
Category: otc | Type: HUMAN OTC DRUG LABEL
Date: 20200629

ACTIVE INGREDIENTS: Niacinamide 0.60 g/30 g; Adenosine 0.01 g/30 g
INACTIVE INGREDIENTS: CENTELLA ASIATICA LEAF; MEDIUM-CHAIN TRIGLYCERIDES

ACTIVE INGREDIENTS

Niacinamide 2.0%, Adenosine 0.04%

INACTIVE INGREDIENTS

Centella Asiatica Leaf Water, Caprylic/Capric Triglyceride, Cetylethyl Hexanoate, Titanium Dioxide, Propylene Glycol , Dimethicone, Hexyl Laurate, Cetyl PEG/PPG-10/1 Dimethicone, 1,2-Hexanediol, Glycerin, Magnesium Sulfate, Sorbitan Sesquioleate, Butylene Glycol, Glutathione, Anemarrhena Asphodeloides Root Extract, Hydrogenated Polyisobutene, Oligopeptide-91 rh-Oligopeptide-1, Palmitoyl Tripeptide-5, sh-Polypeptide-1, Citrus Aurantifolia (Lime) Fruit Extract, Hydrogenated Lecithin, Glycine Soja (Soybean) Sterols, Hydroxydecyl Ubiquinone, Panthenol, Lavandula Angustifolia (Lavender) Oil, Hydroxyethylcellulose, Zinc Stearate, Microcrystalline Wax, Allantoin, Tocopheryl Acetate, Aluminum Hydroxide, Silica Dimethyl Silylate, Iron Oxide (CI 77492), Iron Oxide (CI 77491), Iron Oxide (CI 77499), Talc, Triethoxycaprylylsilane, Disodium EDTA

PURPOSE

Purpose: Skin Brightening, Anti-wrinkle

WARNINGS

1. Consult a physician if red spots, swollenness, itchiness, or any other adnormal symptoms or side effects develops on the applied area during or after use or under direct sunlight.

2. Do not use on wound, etc.
3. Precautions for handling and storage
a) Keep out of the reach of children
b) Avoid direct sunlight

KEEP OUT OF REACH OF CHILDREN

Uses

Helps to brighten the skin.
Helps to improve wrinkles in the skin.

Directions

Mix with the cocktail sun gel or apply to the entire face after use.
Skin effects are proportional to usage and number of times.

QUESTIONS

http://www.incellderm.com